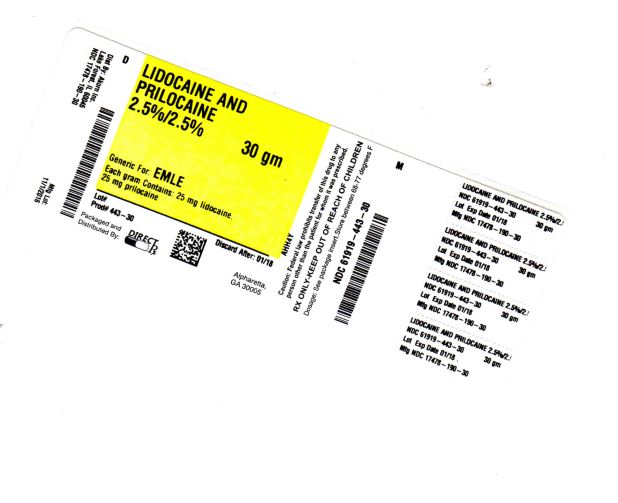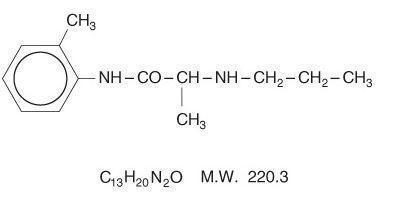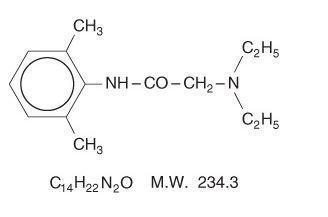 DRUG LABEL: LIDOCAINE AND PRILOCAINE
NDC: 61919-443 | Form: CREAM
Manufacturer: DIRECT RX
Category: prescription | Type: HUMAN PRESCRIPTION DRUG LABEL
Date: 20200120

ACTIVE INGREDIENTS: LIDOCAINE 25 mg/1 g; PRILOCAINE 25 mg/1 g
INACTIVE INGREDIENTS: PEG-55 HYDROGENATED CASTOR OIL; CARBOMER HOMOPOLYMER TYPE B (ALLYL SUCROSE CROSSLINKED); WATER; SODIUM HYDROXIDE

LIDOCAINE AND PRILOCAINE

DESCRIPTION SECTION

Lidocaine 2.5% and Prilocaine 2.5% Cream, USP is an emulsion in which the oil phase is a eutectic mixture of lidocaine and prilocaine cream in a ratio of 1:1 by weight. This eutectic mixture has a melting point below room temperature and therefore both local anesthetics exist as a liquid oil rather than as crystals. It is packaged in 5 gram and 30 gram tubes.

Lidocaine is chemically designated as acetamide, 2-(diethylamino)-N-(2,6-dimethylphenyl), has an octanol: water partition ratio of 43 at pH 7.4, and has the following structure:

Prilocaine is chemically designated as propanamide, N-(2-methylphenyl)-2-(propylamino), has an octanol: water partition ratio of 25 at pH 7.4, and has the following structure:

Each gram of lidocaine and prilocaine cream contains lidocaine 25 mg, prilocaine 25 mg, polyoxyethylene fatty acid esters (as emulsifiers), carboxypolymethylene (as a thickening agent), sodium hydroxide to adjust to a pH approximating 9, and purified water to 1 gram. Lidocaine and prilocaine cream contains no preservative, however it passes the USP antimicrobial effectiveness test due to the pH. The specific gravity of lidocaine and prilocaine cream is 1.00.

CLINICAL PHARMACOLOGY SECTION

Mechanism of Action: Lidocaine and prilocaine cream applied to intact skin under occlusive dressing, provides dermal analgesia by the release of lidocaine and prilocaine from the cream into the epidermal and dermal layers of the skin and by the accumulation of lidocaine and prilocaine in the vicinity of dermal pain receptors and nerve endings. Lidocaine and prilocaine are amide-type local anesthetic agents. Both lidocaine and prilocaine stabilize neuronal membranes by inhibiting the ionic fluxes required for the initiation and conduction of impulses, thereby effecting local anesthetic action.

The onset, depth and duration of dermal analgesia on intact skin provided by lidocaine and prilocaine cream depend primarily on the duration of application. To provide sufficient analgesia for clinical procedures such as intravenous catheter placement and venipuncture, lidocaine and prilocaine cream should be applied under an occlusive dressing for at least 1 hour. To provide dermal analgesia for clinical procedures such as splitskin graft harvesting, lidocaine and prilocaine cream should be applied under occlusive dressing for at least 2 hours. Satisfactory dermal analgesia is achieved 1 hour after application, reaches maximum at 2 to 3 hours, and persists for 1 to 2 hours after removal. Absorption from the genital mucosa is more rapid and onset time is shorter (5 to 10 minutes) than after application to intact skin. After a 5 to 10 minute application of lidocaine and prilocaine cream to female genital mucosa, the average duration of effective analgesia to an argon laser stimulus (which produced a sharp, pricking pain) was 15 to 20 minutes (individual variations in the range of 5 to 45 minutes).

Dermal application of lidocaine and prilocaine cream may cause a transient, local blanching followed by a transient, local redness or erythema.

Pharmacokinetics: Lidocaine and prilocaine cream is a eutectic mixture of lidocaine 2.5% and prilocaine 2.5% formulated as an oil in water emulsion. In this eutectic mixture, both anesthetics are liquid at room temperature (see DESCRIPTION) and the penetration and subsequent systemic absorption of both prilocaine and lidocaine are enhanced over that which would be seen if each component in crystalline form was applied separately as a 2.5% topical cream.

Absorption: The amount of lidocaine and prilocaine systemically absorbed from lidocaine and prilocaine cream is directly related to both the duration of application and to the area over which it is applied. In two pharmacokinetic studies, 60 g of lidocaine and prilocaine cream (1.5 g lidocaine and 1.5 g prilocaine) was applied to 400 cm2 of intact skin on the lateral thigh and then covered by an occlusive dressing. The subjects were then randomized such that one-half of the subjects had the occlusive dressing and residual cream removed after 3 hours, while the remainder left the dressing in place for 24 hours. The results from these studies are summarized below.

TABLE 1 Absorption of Lidocaine and Prilocaine from Lidocaine and Prilocaine Cream: Normal Volunteers (N=16)
Lidocaine and Prilocaine Cream (g) | Area (cm2) | Time on (hrs) | Drug Content (mg) | Absorbed (mg) | Cmax (μg/mL) | Tmax (hr)
60 | 400 | 3 | lidocaine 1500 | 54 | 0.12 | 4
 |  |  | prilocaine 1500 | 92 | 0.07 | 4
60 | 400 | 24* | lidocaine 1500 | 243 | 0.28 | 10
 |  |  | prilocaine 1500 | 503 | 0.14 | 10
*Maximum recommended duration of exposure is 4 hours.

When 60 g of lidocaine and prilocaine cream was applied over 400 cm2 for 24 hours, peak blood levels of lidocaine are approximately 1/20 the systemic toxic level. Likewise, the maximum prilocaine level is about 1/36 the toxic level. In a pharmacokinetic study, lidocaine and prilocaine cream was applied to penile skin in 20 adult male patients in doses ranging from 0.5 g to 3.3 g for 15 minutes. Plasma concentrations of lidocaine and prilocaine following lidocaine and prilocaine cream application in this study were consistently low (2.5 to 16 ng/mL for lidocaine and 2.5 to 7 ng/mL for prilo caine). The application of lidocaine and prilocaine cream to broken or inflamed skin, or to 2,000 cm2 or more of skin where more of both anesthetics are absorbed, could result in higher plasma levels that could, in susceptible individuals, produce a systemic pharmacologic response.

The absorption of lidocaine and prilocaine cream applied to genital mucous membranes was studied in two open-label clinical trials. Twenty-nine patients received 10 g of lidocaine and prilocaine cream applied for 10 to 60 minutes in the vaginal fornices. Plasma concentrations of lidocaine and prilocaine following lidocaine and prilocaine cream application in these studies ranged from 148 to 641 ng/mL for lidocaine and 40 to 346 ng/mL for prilocaine and time to reach maximum concentration (tmax) ranged from 21 to 125 minutes for lidocaine and from 21 to 95 minutes for prilocaine. These levels are well below the concentrations anticipated to give rise to systemic toxicity (approximately 5000 ng/mL for lidocaine and prilocaine).

Distribution: When each drug is administered intravenously, the steady-state volume of distribution is 1.1 to 2.1 L/kg (mean 1.5, ±0.3 SD, n=13) for lidocaine and is 0.7 to 4.4 L/kg (mean 2.6, ±1.3 SD, n=13) for prilocaine. The larger distribution volume for prilocaine produces the lower plasma concentrations of prilocaine observed when equal amounts of prilocaine and lidocaine are administered. At concentrations produced by application of lidocaine and prilocaine cream, lidocaine is approximately 70% bound to plasma proteins, primarily alpha-1-acid glycoprotein. At much higher plasma concentrations (1 to 4 μg/mL of free base) the plasma protein binding of lidocaine is concentration dependent. Prilocaine is 55% bound to plasma proteins. Both lidocaine and prilocaine cross the placental and blood brain barrier, presumably by passive diffusion.

Metabolism: It is not known if lidocaine or prilocaine are metabolized in the skin. Lidocaine is metabolized rapidly by the liver to a number of metabolites including monoethylglycinexylidide (MEGX) and glycinexylidide (GX), both of which have pharmacologic activity similar to, but less potent than that of lidocaine. The metabolite, 2,6-xylidine, has unknown pharmacologic activity. Following intravenous administration, MEGX and GX concentrations in serum range from 11 to 36% and from 5 to 11% of lidocaine concentrations, respectively. Prilocaine is metabolized in both the liver and kidneys by amidases to various metabolites including ortho-toluidine and N-n-propylalanine. It is not metabolized by plasma esterases. The ortho-toluidine metabolite has been shown to be carcinogenic in several animal models (see Carcinogenesis subsection of PRECAUTIONS). In addition, ortho-toluidine can produce methemoglobinemia following systemic doses of prilocaine approximating 8 mg/kg (see ADVERSE REACTIONS). Very young patients, patients with glucose-6-phosphate dehydro genase deficiencies and patients taking oxidizing drugs such as antimalarials and sulfonamides are more susceptible to methemoglobinemia (see Methemoglobinemia subsection of PRECAUTIONS).

Elimination: The terminal elimination half-life of lidocaine from the plasma following IV administration is approximately 65 to 150 minutes (mean 110, ±24 SD, n=13). More than 98% of an absorbed dose of lidocaine can be recovered in the urine as metabolites or parent drug. The systemic clearance is 10 to 20 mL/min/kg (mean 13, ±3 SD, n=13). The elimination half-life of prilocaine is approximately 10 to 150 minutes (mean 70, ±48 SD, n=13). The systemic clearance is 18 to 64 mL/min/kg (mean 38, ±15 SD, n=13). During intravenous studies, the elimination half-life of lidocaine was statistically significantly longer in elderly patients (2.5 hours) than in younger patients (1.5 hours). No studies are available on the intravenous pharmacokinetics of prilocaine in elderly patients.

Pediatrics: Some pharmacokinetic (PK) data are available in infants (1 month to <2 years old) and children (2 to <12 years old). One PK study was conducted in 9 full-term neonates (mean age: 7 days and mean gestational age: 38.8 weeks). The study results show that neonates had comparable plasma lidocaine and prilocaine concentrations and blood methemoglobin concentrations as those found in previous pediatric PK studies and clinical trials. There was a tendency towards an increase in methemoglobin formation. However, due to assay limitations and very little amount of blood that could be collected from neonates, large variations in the above reported concentrations were found.

Special Populations: No specific PK studies were conducted. The half-life may be increased in cardiac or hepatic dysfunction. Prilocaine's half-life also may be increased in hepatic or renal dysfunction since both of these organs are involved in prilocaine metabolism.

CLINICAL STUDIES SECTION

Lidocaine and prilocaine cream application in adults prior to IV cannulation or venipuncture was studied in 200 patients in four clinical studies in Europe. Application for at least 1 hour provided significantly more dermal analgesia than placebo cream or ethyl chloride. Lidocaine and prilocaine cream was comparable to subcutaneous lidocaine, but was less efficacious than intradermal lidocaine. Most patients found lidocaine and prilocaine cream treatment preferable to lidocaine infiltration or ethyl chloride spray.

Lidocaine and prilocaine cream was compared with 0.5% lidocaine infiltration prior to skin graft harvesting in one open label study in 80 adult patients in England. Application of lidocaine and prilocaine cream for 2 to 5 hours provided dermal analgesia comparable to lidocaine infiltration.

Lidocaine and prilocaine cream application in children was studied in seven non-US studies (320 patients) and one US study (100 patients). In controlled studies, application of lidocaine and prilocaine cream for at least 1 hour with or without presurgical medication prior to needle insertion provided significantly more pain reduction than placebo. In children under the age of seven years, lidocaine and prilocaine cream was less effective than in older children or adults.

Lidocaine and prilocaine cream was compared with placebo in the laser treatment of facial port-wine stains in 72 pediatric patients (ages 5 to 16). lidocaine and prilocaine cream was effective in providing pain relief during laser treatment.

Lidocaine and prilocaine cream alone was compared with lidocaine and prilocaine cream followed by lidocaine infiltration and lidocaine infiltration alone prior to cryotherapy for the removal of male genital warts. The data from 121 patients demonstrated that lidocaine and prilocaine cream was not effective as a sole anesthetic agent in managing the pain from the surgical procedure. The administration of lidocaine and prilocaine cream prior to lidocaine infiltration provided significant relief of discomfort associated with local anesthetic infiltration and thus was effective in the overall reduction of pain from the procedure only when used in conjunction with local anesthetic infiltration of lidocaine.

Lidocaine and prilocaine cream was studied in 105 full term neonates (gestational age: 37 weeks) for blood drawing and circumcision procedures. When considering the use of lidocaine and prilocaine cream in neonates, the primary concerns are the systemic absorption of the active ingredients and the subsequent formation of methemoglobin. In clinical studies performed in neonates, the plasma levels of lidocaine, prilocaine, and methemoglobin were not reported in a range expected to cause clinical symptoms.

Local dermal effects associated with lidocaine and prilocaine cream application in these studies on intact skin included paleness, redness and edema and were transient in nature (see ADVERSE REACTIONS).

The application of lidocaine and prilocaine cream on genital mucous membranes for minor, superficial surgical procedures (eg, removal of condylomata acuminata) was studied in 80 patients in a placebo-controlled clinical trial (60 patients received lidocaine and prilocaine cream and 20 patients received placebo). Lidocaine and prilocaine cream (5 to 10 g) applied between 1 and 75 minutes before surgery, with a median time of 15 minutes, provided effective local anesthesia for minor superficial surgical procedures. The greatest extent of analgesia, as measured by VAS scores, was attained after 5to 15 minutes' application. The application of lidocaine and prilocaine cream to genital mucous membranes as pretreatment for local anesthetic infiltration was studied in a double-blind, placebo-controlled study in 44 female patients (21 patients received lidocaine and prilocaine cream and 23 patients received placebo) scheduled for infiltration prior to a surgical procedure of the external vulva or genital mucosa. Lidocaine and prilocaine cream applied to the genital mucous membranes for 5 to 10 minutes resulted in adequate topical anesthesia for local anesthetic injection.

Individualization of Dose: The dose of lidocaine and prilocaine cream that provides effective analgesia depends on the duration of the application over the treated area.

All pharmacokinetic and clinical studies employed a thick layer of lidocaine and prilocaine cream (1 to 2 g/ 10 cm2). The duration of application prior to venipuncture was 1 hour. The duration of application prior to taking split thickness skin grafts was 2 hours. A thinner application has not been studied and may result in less complete analgesia or a shorter duration of adequate analgesia.

The systemic absorption of lidocaine and prilocaine is a side effect of the desired local effect. The amount of drug absorbed depends on surface area and duration of application. The systemic blood levels depend on the amount absorbed and patient size (weight) and the rate of systemic drug elimination. Long duration of application, large treatment area, small patients, or impaired elimination may result in high blood levels. The systemic blood levels are typically a small fraction (1/20 to 1/36) of the blood levels that produce toxicity. Table 2 below gives maximum recommended doses, application areas and application times for infants and children.

TABLE 2 LIDOCAINE AND PRILOCAINE CREAM MAXIMUM RECOMMENDED DOSE, APPLICATION AREA, AND APPLICATION TIME BY AGE AND WEIGHT* For Infants and Children Based on Application to Intact Skin
Age and Body Weight Requirements | Maximum Total Dose of lidocaine and prilocaine cream | Maximum Application Area** | Maximum Application Time
0 up to 3 months or < 5 kg | 1 g | 10 cm2 | 1 hour
3 up to 12 months and > 5 kg | 2 g | 20 cm2 | 4 hours
1 to 6 years and > 10 kg | 10 g | 100 cm2 | 4 hours
7 to 12 years and > 20 kg | 20 g | 200 cm2 | 4 hours
Please note: If a patient greater than 3 months old does not meet the minimum weight requirement, the maximum total dose of lidocaine and prilocaine cream should be restricted to that which corresponds to the patient's weight.
* These are broad guidelines for avoiding systemic toxicity in applying lidocaine and prilocaine cream to patients with normal intact skin and with normal renal and hepatic function.
** For more individualized calculation of how much lidocaine and prilocaine may be absorbed, physicians can use the following estimates of lidocaine and prilocaine absorption for children and adults:
The estimated mean (±SD) absorption of lidocaine is 0.045 (±0.016) mg/cm2/hr.
The estimated mean (±SD) absorption of prilocaine is 0.077 (±0.036) mg/cm2/hr.

An I.V. antiarrhythmic dose of lidocaine is 1 mg/kg (70 mg/70 kg) and gives a blood level of about 1 μg/mL. Toxicity would be expected at blood levels above 5 μg/mL. Smaller areas of treatment are recommended in a debilitated patient, a small child or a patient with impaired elimination. Decreasing the duration of application is likely to decrease the analgesic effect.

INDICATIONS & USAGE SECTION

Lidocaine and prilocaine cream (a eutectic mixture of lidocaine 2.5% and prilocaine 2.5%) is indicated as a topical anesthetic for use on:

-normal intact skin for local analgesia.-genital mucous membranes for superficial minor surgery and as pretreatment for infiltration anesthesia.

lidocaine and prilocaine cream is not recommended in any clinical situation when penetration or migration beyond the tympanic membrane into the middle ear is possible because of the ototoxic effects observed in animal studies (see WARNINGS).

CONTRAINDICATIONS SECTION

Lidocaine and prilocaine cream (lidocaine 2.5% and prilocaine 2.5%) is contraindicated in patients with a known history of sensitivity to local anesthetics of the amide type or to any other component of the product.

WARNINGS SECTION

Application of lidocaine and prilocaine cream to larger areas or for longer times than those recommended could result in sufficient absorption of lidocaine and prilocaine resulting in serious adverse effects (see Individualization of Dose).

Patients treated with class III anti-arrhythmic drugs (et, amiodarone, bretylium, sotalol, dofetilide) should be under close surveillance and ECG monitoring considered, because cardiac effects may be additive.

Studies in laboratory animals (guinea pigs) have shown that lidocaine and prilocaine cream has an ototoxic effect when instilled into the middle ear. In these same studies, animals exposed to lidocaine and prilocaine cream only in the external auditory canal, showed no abnormality. Lidocaine and prilocaine cream should not be used in any clinical situation when its penetration or migration beyond the tympanic membrane into the middle ear is possible.

Methemoglobinemia: lidocaine and prilocaine cream should not be used in those rare patients with congenital or idiopathic methemoglobinemia and in infants under the age of twelve months who are receiving treatment with methemoglobin-inducing agents.

Very young patients or patients with glucose-6-phosphate dehydrogenase deficiencies are more susceptible to methemoglobinemia.

Patients taking drugs associated with drug-induced methemoglobinemia such as sulfonamides, acetaminophen, acetanilid, aniline dyes, benzocaine, chloroquine, dapsone, naphthalene, nitrates and nitrites, nitrofurantoin, nitroglycerin, nitroprusside, pamaquine, para-aminosalicylic acid, phenacetin, phenobarbital, phenytoin, primaquine, quinine, are also at greater risk for developing methemoglobinemia.

There have been reports of significant methemoglobinemia (20 to 30%) in infants and children following excessive applications of lidocaine and prilocaine cream. These cases involved the use of large doses, larger than recommended areas of application, or infants underthe age of 3 months who did not have fully mature enzyme systems. In addition, a few of these cases involved the concomitant administration of methemoglobin-inducing agents. Most patients recovered spontaneously after removal of the cream. Treatment with IV methylene blue may be effective if required.

Physicians are cautioned to make sure that parents orother caregivers understand the need for careful application of lidocaine and prilocaine cream, to ensure that the doses and areas of application recommended in Table 2 are not exceeded (especially in children under the age of 3 months) and to limit the period of application to the minimum required to achieve the desired anesthesia.

Neonates and infants up to 3 months of age should be monitored for Met-Hb levels before, during, and after the application of lidocaine and prilocaine cream, provided the test results can be obtained quickly.

PRECAUTIONS SECTION

General: Repeated doses of lidocaine and prilocaine cream may increase blood levels of lidocaine and prilocaine. Lidocaine and prilocaine cream should be used with caution in patients who may be more sensitive to the systemic effects of lidocaine and prilocaine including acutely ill, debilitated, or elderly patients.

Lidocaine and prilocaine cream should not be applied to open wounds.

Care should be taken not to allow lidocaine and prilocaine cream to come in contact with the eye because animal studies have demonstrated severe eye irritation. Also the loss of protective reflexes can permit corneal irritation and potential abrasion. Absorption of lidocaine and prilocaine cream in conjunctival tissues has not been determined. If eye contact occurs, immediately wash out the eye with water or saline and protect the eye until sensation returns.

Patients allergic to paraaminobenzoic acid derivatives (procaine, tetracaine, benzocaine, etc.) have not shown cross sensitivity to lidocaine and/or prilocaine, however, lidocaine and prilocaine cream should be used with caution in patients with a history of drug sensitivities, especially if the etiologic agent is uncertain.

Patients with severe hepatic disease, because of their inability to metabolize local anesthetics normally, are at greater risk of developing toxic plasma concentrations of lidocaine and prilocaine.

Lidocaine and prilocaine have been shown to inhibit viral and bacterial growth. The effect of lidocaine and prilocaine cream on intradermal injections of live vaccines has not been determined.

Information for Patients: When lidocaine and prilocaine cream is used, the patient should be aware that the production of dermal analgesia may be accompanied by the block of all sensations in the treated skin. For this reason, the patient should avoid inadvertent trauma to the treated area by scratching, rubbing, or exposure to extreme hot or cold temperatures until complete sensation has returned.

Lidocaine and prilocaine cream should not be applied near the eyes or on open wounds.

Drug Interactions: Lidocaine and prilocaine cream should be used with caution in patients receiving Class I antiarrhythmic drugs (such as tocainide and mexiletine) since the toxic effects are additive and potentially synergistic.

Prilocaine may contribute to the formation of methemoglobin in patients treated with other drugs known to cause this condition (see Methemoglobinemia subsection of WARNINGS).

Specific interaction studies with lidocaine/prilocaine and class III anti-arrhythmic drugs (eg, amiodarone, bretylium, sotalol, doetilide) have not been performed, but caution is advised (see WARNINGS).

Should lidocaine and prilocaine cream be used concomitantly with other products containing lidocaine and/or prilocaine, cumulative doses from all formulations must be considered.

Carcinogenesis, Mutagenesis, Impairment of Fertility

Carcinogenesis: Long-term studies in animals designed to evaluate the carcinogenic potential of lidocaine and prilocaine have not been conducted.

Metabolites of prilocaine have been shown to be carcinogenic in laboratory animals. In the animal studies reported below, doses or blood levels are compared with the Single Dermal Administration (SDA) of 60 g of lidocaine and prilocaine cream to 400 cm2 for 3 hours to a small person (50 kg). The typical application of lidocaine and prilocaine cream for one or two treatments for venipuncture sites (2.5 or 5 g) would be 1/24 or 1/12 of that dose in an adult or about the same mg/kg dose in an infant.

Chronic oral toxicity studies of ortho-toluidine, a metabolite of prilocaine, in mice (450 to 7200 mg/m2; 60 to 960 times SDA) and rats (900 to 4,800 mg/m2; 60 to 320 times SDA) have shown that ortho-toluidine is a carcinogen in both species. The tumors included hepatocarcinomas/adenomas in female mice, multiple occurrences of hemangiosarcomas/hemangiomas in both sexes of mice, sarcomas of multiple organs, transitional-cell carcinomas/papillomas of urinary bladder in both sexes of rats, subcutaneous fibromas/fibrosarcomas and mesotheliomas in male rats, and mammary gland fibroadenomas/adenomas in female rats. The lowest dose tested (450 mg/m2 in mice, 900 mg/m2 in rats; 60 times SDA) was carcinogenic in both species. Thus the no-effect dose must be less than 60 times SDA. The animal studies were conducted at 150 to 2,400 mg/kg in mice and at 150 to 800 mg/kg in rats. The dosages have been converted to mg/m2 for the SDA calculations above.

Mutagenesis: The mutagenic potential of lidocaine HCl has been tested in a bacterial reverse (Ames) assay in Salmonella, an in vitro chromosomal aberration assay using human lymphocytes an in vivo micronucleus test in mice. There was no indication of mutagenicity or structural damage to chromosomes in these tests.

Ortho-toluidine, a metabolite of prilocaine, at a concentration of 0.5 μg/mL, was genotoxic in Escherichia coli DNA repair and phage-induction assays. Urine concentrates from rats treated with ortho-toluidine (300 mg/kg orally; 300 times SDA) were mutagenic when examined in Salmonella typftimurium in the presence of metabolic activation. Several other tests on ortho-toluidine, including reverse mutations in five different Salmonella typftimurium strains in the presence or absence of metabolic activation and a study to detect single strand breaks in DNA of V79 Chinese hamster cells, were negative.

Impairment of Fertility: See Use in Pregnancy.

Use in Pregnancy: Teratogenic Effects: Pregnancy Category B.

Reproduction studies with lidocaine have been performed in rats and have revealed no evidence of harm to the fetus (30 mg/kg subcutaneously; 22 times SDA). Reproduction studies with prilocaine have been performed in rats and have revealed no evidence of impaired fertility or harm to the fetus (300 mg/kg intramuscularly; 188 times SDA). There are, however, no adequate and well-controlled studies in pregnant women. Because animal reproduction studies are not always predictive of human response, lidocaine and prilocaine cream should be used during pregnancy only if clearly needed.

Reproduction studies have been performed in rats receiving subcutaneous administration of an aqueous mixture containing lidocaine HCl and prilocaine HCl at 1:1 (w/w). At 40 mg/kg each, a dose equivalent to 29 times SDA lidocaine and 25 times SDA prilocaine, no teratogenic, embryotoxic or fetotoxic effects were observed.

Labor and Delivery: Neither lidocaine nor prilocaine are contraindicated in labor and delivery. Should lidocaine and prilocaine cream be used concomitantly with other products containing lidocaine and/or prilocaine, cumulative doses from all formulations must be considered.

Nursing Mothers: Lidocaine, and probably prilocaine, are excreted in human milk. Therefore, caution should be exercised when lidocaine and prilocaine cream is administered to a nursing mother since the milk:plasma ratio of lidocaine is 0.4 and is not determined for prilocaine.

Pediatric Use: Controlled studies of lidocaine and prilocaine cream in children under the age of seven years have shown less overall benefit than in older children or adults. These results illustrate the importance ofemotional and psychological support of younger children undergoing medical or surgical procedures.

Lidocaine and prilocaine cream should be used with care in patients with conditions or therapy associated with methemoglobinemia (see Methemoglobinemia subsection of WARNINGS).

When using lidocaine and prilocaine cream in young children, especially infants under the age of 3 months, care must be taken to insure that the caregiver understands the need to limit the dose and area of application, and to prevent accidental ingestion (see DOSAGE AND ADMINISTRATION and Methemoglobinemia).

In neonates (minimum gestation age: 37 weeks) and children weighing less than 20 kg, the area and duration of application should be limited (see TABLE 2 in Individualization of Dose).

Studies have not demonstrated the efficacy of lidocaine and prilocaine cream for heel lancing in neonates.

Geriatric Use: Of the total number of patients in clinical studies of lidocaine and prilocaine cream, 180 were age 65 to 74 and 138 were 75 and over. No overall differences in safety or efficacy were observed between these patients and younger patients. Other reported clinical experience has not identified differences in responses between the elderly and younger patients, but greater sensitivity of some older individuals cannot be ruled out.

Plasma levels of lidocaine and prilocaine in geriatric and non-geriatric patients following application of a thick layer of lidocaine and prilocaine cream are very low and well below potentially toxic levels. However, there are no sufficient data to evaluate quantitative differences in systemic plasma levels of lidocaine and prilocaine between geriatric and non-geriatric patients following application of lidocaine and prilocaine cream.

Consideration should be given for those elderly patients who have enhanced sensitivity to systemic absorption (see PRECAUTIONS).

After intravenous dosing, the elimination half-life of lidocaine is significantly longer in elderly patients (2.5 hours) than in younger patients (1.5 hours). (See CLINICAL PHARMACOLOGY).

ADVERSE REACTIONS SECTION

Localized Reactions: During or immediately after treatment with lidocaine and prilocaine cream on intact skin, the skin at the site of treatment may develop erythema or edema or may be the locus of abnormal sensation. Rare cases of discrete purpuric or petechial reactions at the application site have been reported. Rare cases of hyperpigmentation following the use of lidocaine and prilocaine cream have been reported. The relationship to lidocaine and prilocaine cream or the underlying procedure has not been established. In clinical studies on intact skin involving over 1,300 lidocaine and prilocaine cream-treated subjects, one or more such local reactions were noted in 56% of patients, and were generally mild and transient, resolving spontaneously within 1 or 2 hours. There were no serious reactions that were ascribed to lidocaine and prilocaine cream.

Two recent reports describe blistering on the foreskin in neonates about to undergo circumcision. Both neonates received 1.0 g of lidocaine and prilocaine cream.

In patients treated with lidocaine and prilocaine cream on intact skin, local effects observed in the trials included: paleness (pallor or blanching) 37%, redness (erythema) 30%, alterations in temperature sensations 7%, edema 6%, itching 2% and rash, less than 1%.

In clinical studies on genital mucous membranes involving 378 lidocaine and prilocaine cream-treated patients, one or more application site reactions, usually mild and transient, were noted in 41% of patients. The most common application site reactions were redness (21%), burning sensation (17%) and edema (10%).

Allergic Reactions: Allergic and anaphylactoid reactions associated with lidocaine or prilocaine can occur. They are characterized by urticaria, angioedema, bronchospasm, and shock. If they occur they should be managed by conventional means. The detection of sensitivity by skin testing is of doubtful value.

Systemic (Dose Related) Reactions: Systemic adverse reactions following appropriate use of lidocaine and prilocaine cream are unlikely due to the small dose absorbed (see Pharmacokinetics subsection of CLINICAL PHARMACOLOGY). Systemic adverse effects of lidocaine and/or prilocaine are similar in nature to those observed with other amide local anesthetic agents including CNS excitation and/or depression (light-headedness, nervousness, apprehension, euphoria, confusion, dizziness, drowsiness, tinnitus, blurred or double vision, vomiting, sensations of heat, cold or numbness, twitching, tremors, convulsions, unconsciousness, respiratory depression and arrest). Excitatory CNS reactions may be brief or not occur at all, in which case the first manifestation may be drowsiness merging into unconsciousness. Cardiovascular manifestations may include bradycardia, hypotension and cardiovascular collapse leading to arrest.

OVERDOSAGE SECTION

Peak blood levels following a 60 g application to 400 cm2 of intact skin for 3 hours are 0.05 to 0.16 μg/mL for lidocaine and 0.02 to 0.10 μg/mL for prilocaine. Toxic levels of lidocaine (>5 μg/mL) and/or prilocaine (>6 μg/mL) cause decreases in cardiac output, total peripheral resistance and mean arterial pressure. These changes may be attributable to direct depressant effects of these local anesthetic agents on the cardiovascular system. In the absence of massive topical overdose or oral ingestion, evaluation should include evaluation of other etiologies for the clinical effects or overdosage from other sources of lidocaine, prilocaine or other local anesthetics. Consult the package inserts for parenteral Xylocaine (lidocaine HCl) or Citanest (prilocaine HCl) for further information for the management of overdose.

DOSAGE & ADMINISTRATION SECTION

Adult Patients-Intact Skin

A thick layer of lidocaine and prilocaine cream is applied to intact skin and covered with an occlusive dressing (see INSTRUCTIONS FOR APPLICATION).

Minor Dermal Procedures: For minor procedures such as intravenous cannulation and venipuncture, apply 2.5 grams of lidocaine and prilocaine cream (1/2 the 5 g tube) over 20 to 25 cm2 of skin surface for at least 1 hour. In controlled clinical trials using lidocaine and prilocaine cream, two sites were usually prepared in case there was a technical problem with cannulation or venipuncture at the first site.

Major Dermal Procedures: For more painful dermatological procedures involving a larger skin area such as split thickness skin graft harvesting, apply 2 grams of lidocaine and prilocaine cream per 10 cm2 of skin and allow to remain in contact with the skin for at least 2 hours.

Adult Male Genital Skin: As an adjunct prior to local anesthetic infiltration, apply a thick layer of lidocaine and prilocaine cream (1 g/10 cm2) to the skin surface for 15 minutes. Local anesthetic infiltration should be performed immediately after removal of lidocaine and prilocaine cream.

Dermal analgesia can be expected to increase for up to 3 hours under occlusive dressing and persist for 1 to 2 hours after removal of the cream. The amount of lidocaine and prilocaine absorbed during the period of application can be estimated from the information in Table 2, ** footnote, in Individualization of Dose.

Adult Female Patients-Genital Mucous Membranes

For minor procedures on the female external genitalia, such as removal of condylomata acuminata, as well as for use as pretreatment for anesthetic infiltration, apply a thick layer (5 to 10 grams) of lidocaine and prilocaine cream for 5 to 10 minutes.

Occlusion is not necessary for absorption, but may be helpful to keep the cream in place. Patients should be lying down during the lidocaine and prilocaine cream application, especially if no occlusion is used. The procedure or the local anesthetic infiltration should be performed immediately after the removal of lidocaine and prilocaine cream.

Pediatric Patients-Intact Skin

The following are the maximum recommended doses, application areas and application times for lidocaine and prilocaine cream based on a child's age and weight:

Age and Body Weight Requirements | Maximum Total Dose of Lidocaine and Prilocaine Cream | Maximum Application Area | Maximum Application Time
0 up to 3 months or < 5 kg | 1 g | 10 cm2 | 1 hour
3 up to 12 months and > 5 kg | 2 g | 20 cm2 | 4 hours
1 to 6 years and > 10 kg | 10 g | 100 cm2 | 4 hours
7 to 12 years and 20 kg | 20 g | 200 cm2 | 4 hours

Please note: If a patient greater than 3 months old does not meet the minimum weight requirement, the maximum total dose of lidocaine and prilocaine cream should be restricted to that which corresponds to the patient's weight (see INSTRUCTIONS FOR APPLICATION).

Practitioners should carefully instruct caregivers to avoid application of excessive amounts of lidocaine and prilocaine cream (see PRECAUTIONS).

When applying lidocaine and prilocaine cream to the skin of young children, care must be taken to maintain careful observation of the child to prevent accidental ingestion of lidocaine and prilocaine cream or the occlusive dressing. A secondary protective covering to prevent inadvertent disruption of the application site may be useful.

Lidocaine and prilocaine cream should not be used in neonates with a gestational age less than 37 weeks nor in infants under the age of 12 months who are receiving treatment with methemoglobin-inducing agents (see Methemoglobinemia subsection of WARNINGS).

When lidocaine and prilocaine cream (lidocaine 2.5% and prilocaine 2.5%) is used concomitantly with other products containing local anesthetic agents, the amount absorbed from all formulations must be considered (see Individualization of Dose). The amount absorbed in the case of lidocaine and prilocaine cream is determined by the area over which it is applied and the duration of application under occlusion (see Table 2, ** footnote, in Individualization of Dose).

Although the incidence of systemic adverse reactions with lidocaine and prilocaine cream is very low, caution should be exercised, particularly when applying it over large areas and leaving it on for longer than 2 hours. The incidence of systemic adverse reactions can be expected to be directly proportional to the area and time of exposure (see Individualization of Dose).

INSTRUCTIONS FOR USE SECTION

To measure 1 gram of lidocaine and prilocaine cream, the Cream should be gently squeezed out of the tube as a narrow strip that is 1.5 inches (3.8 cm) long and 0.2 inches (5 mm) wide. The strip of lidocaine and prilocaine cream should be contained within the lines of the diagram shown below.

Use the number of strips that equals your dose, like the examples in the table below.

Dosing Information

1 gram = 1 strip

2 grams = 2 strips

2.5 grams = 2.5 strips

For adult and pediatric patients, apply ONLY as prescribed by your physician.

If your child is below the age of 3 months or small for their age, please inform your doctor before applying lidocaine and prilocaine cream, which can be harmful, if applied over too much skin at one time in young children.

When applying lidocaine and prilocaine cream to the intact skin of young children, it is important that they be carefully observed by an adult in order to prevent the accidental ingestion of or eye contact with lidocaine and prilocaine cream.

lidocaine and prilocaine cream must be applied to intact skin at least 1 hour before the start of a routine procedure and for 2 hours before the start of a painful procedure. A protective covering of the cream is not necessary for absorption but may be helpful to keep the cream in place.

If using a protective covering, your doctor will remove it, wipe off the lidocaine and prilocaine cream, and clean the entire area with an antiseptic solution before the procedure. The duration of effective skin anesthesia will be at least 1 hour after removal of the protective covering.

Precautions

1. Do not apply near eyes or open wounds.
2. Keep out of the reach of children.
3. If your child becomes very dizzy, excessively sleepy, or develops duskiness of the face or lips after applying lidocaine and prilocaine cream, remove the cream and contact the child's physician at once.

HOW SUPPLIED SECTION

Lidocaine 2.5% and Prilocaine 2.5% Cream, USP is available as the following:

NDC No. | Strength | Size
NDC 17478-190-05 | 5 gram/tube | packed individually.
NDC 17478-190-55 | 5 gram/tube | packed in 5.
NDC 17478-190-30 | 30 gram/tube | packed individually, in a child-resistant tube.

NOT FOR OPHTHALMIC USE.

KEEP CONTAINER TIGHTLY CLOSED AT ALL TIMES WHEN NOT IN USE.

Storage: Store at 20° to 25°C (68° to 77°F)[see USP Controlled Room Temperature].

AKORN

Distributed by: Akorn, Inc.

Lake Forest, IL 60045

LN00N

Rev. 06/12

Principal Display Panel Text for Container Label:

NDC 17478-190-05 5 grams

Lidocaine 2.5% and

Prilocaine 2.5% Cream, USP

Rx only Akorn Logo